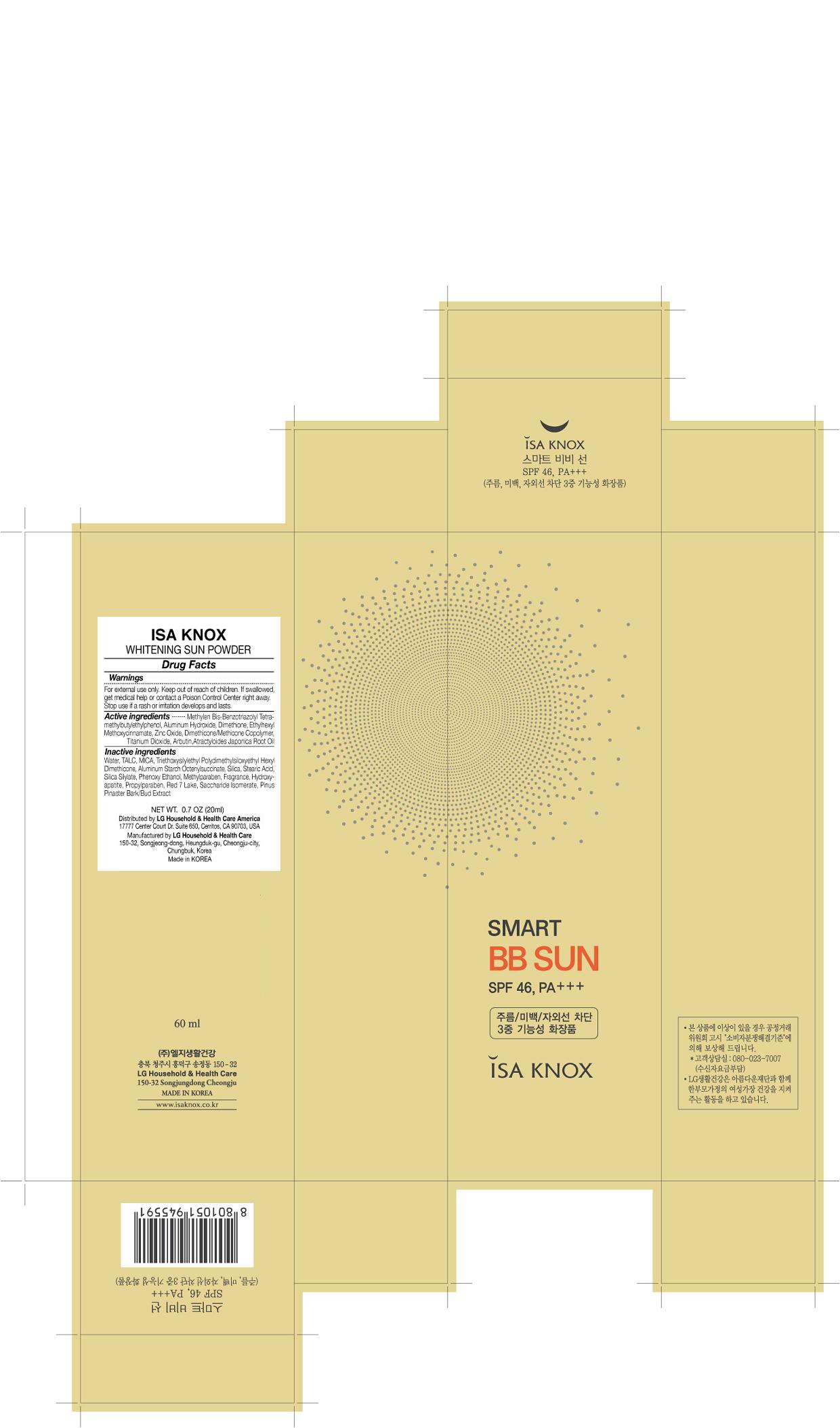 DRUG LABEL: ISA KNOX SMART BB SUN
NDC: 53208-520 | Form: CREAM
Manufacturer: LG Household and Healthcare, Inc.
Category: otc | Type: HUMAN OTC DRUG LABEL
Date: 20110412

ACTIVE INGREDIENTS: OCTINOXATE 7 mL/100 mL; TITANIUM DIOXIDE 6.72 mL/100 mL; ZINC OXIDE 2.88 mL/100 mL; HYDROXYPROLINE 0.5 mL/100 mL; ATRACTYLODES JAPONICA ROOT OIL 0.05 mL/100 mL
INACTIVE INGREDIENTS: WATER; BUTYLENE GLYCOL; DIMETHICONE; ENSULIZOLE; TRISILOXANE; METHYL TRIMETHICONE; TROMETHAMINE; HECTORITE; MAGNESIUM SULFATE, UNSPECIFIED; PANTHENOL; IRON; PHENOXYETHANOL; METHYLPARABEN; DISTEARYLDIMONIUM CHLORIDE; STEARIC ACID; ACETATE ION; FERRIC OXIDE RED; FERROSOFERRIC OXIDE; PROPYLPARABEN; CANNA INDICA ROOT; SACCHARIDE ISOMERATE; MARITIME PINE

Drug Facts

ACTIVE INGREDIENT

OCTINOXATE 7%

TITANIUM DIOXIDE 6.72%

ZINC OXIDE 2.88%

HYDROXYPROLINE 0.5 %

ATRACTYLODES JAPONICA ROOT OIL 0.05%

WARNINGS AND PRECAUTIONS

For external use only.

Keep out of reach of children. Is swallowed, get medical help or contact a Poison Control Center right away.

WHEN USING

Keep out of eyes. Rinse with water to remove.

Stop use if a rash or irritation develops and lasts.